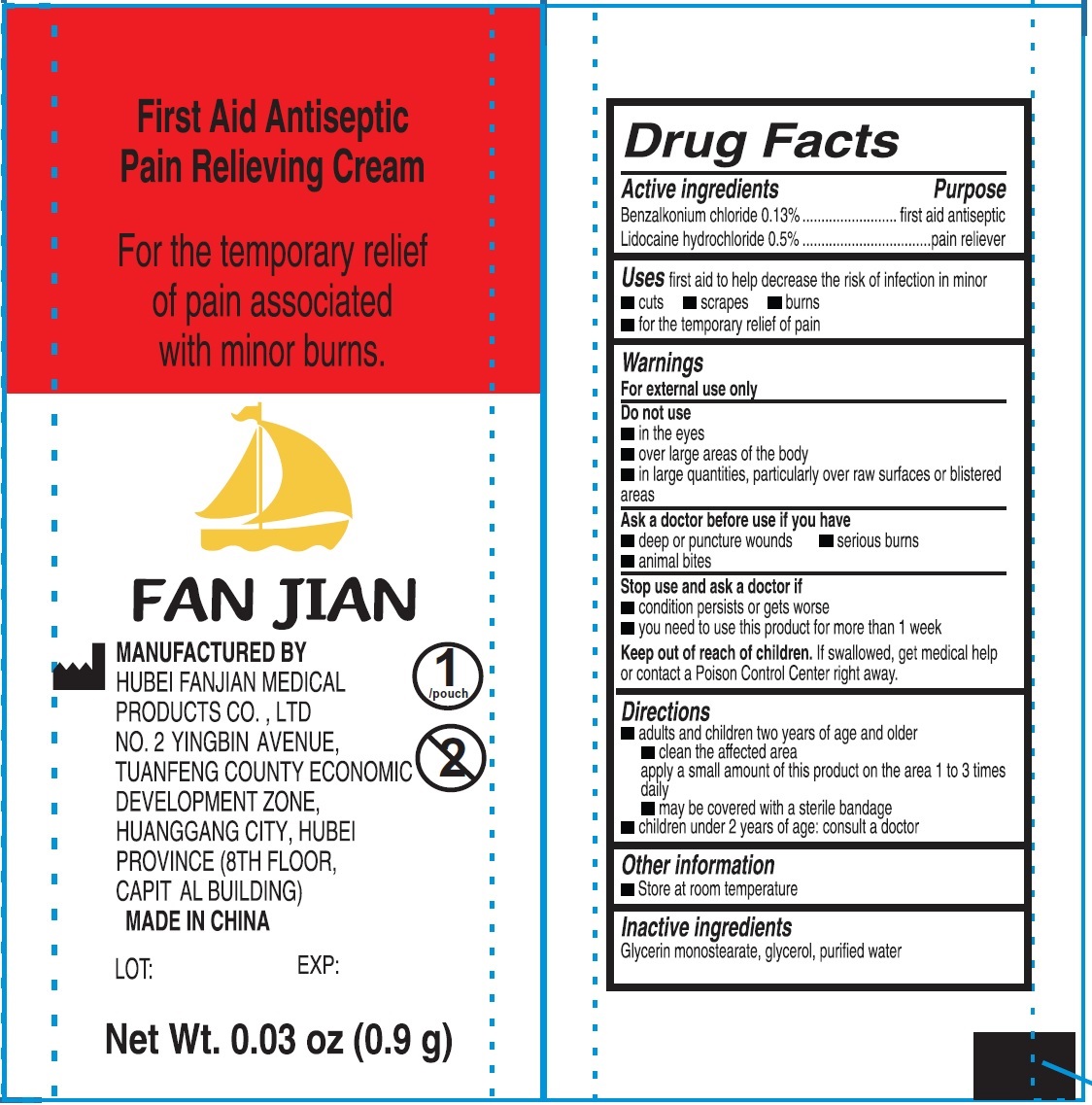 DRUG LABEL: First Aid Antiseptic Pain Relieving Cream
NDC: 83165-004 | Form: LIQUID
Manufacturer: Hubei Fanjian Medical Product Co.,Ltd
Category: otc | Type: HUMAN OTC DRUG LABEL
Date: 20231110

ACTIVE INGREDIENTS: BENZALKONIUM CHLORIDE 1.3 mg/1 g; LIDOCAINE HYDROCHLORIDE 5 mg/1 g
INACTIVE INGREDIENTS: GLYCERYL MONOSTEARATE; GLYCERIN; WATER

First Aid Antiseptic Pain Relieving Cream

Active ingredients

Benzalkonium chloride 0.13%

Lidocaine hydrochloride 0.5%

Purpose

first aid antiseptic

pain reliever

Uses

first aid to help decrease the risk of infection in minor

• cuts • scrapes • burns • for the temporary relief of pain

Warnings

For external use only

Do not use

• in the eyes

• over large areas of the body

• in large quantities, particularly over raw surfaces or blistered areas

Ask a doctor before use if you have

• deep or puncture wounds • serious burns • animal bites

Stop use and ask a doctor if

• condition persists or gets worse

• you need to use this product for more than 1 week

Keep out of reach of children.

If swallowed, get medical help or contact a Poison Control Center right away.

Directions

• adults and children two years of age and older

• clean the affected area apply a small amount of this product on the area 1 to 3 times daily

• may be covered with a sterile bandage

• children under 2 years of age: consult a doctor

Other information

• Store at room temperature

Inactive ingredients

Glycerin monostearate, glycerol, purified water